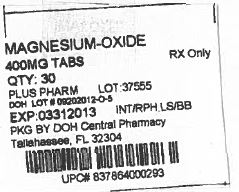 DRUG LABEL: Magnesium Oxide
NDC: 53808-0684 | Form: TABLET
Manufacturer: State of Florida DOH Central Pharmacy
Category: otc | Type: HUMAN OTC DRUG LABEL
Date: 20130925

ACTIVE INGREDIENTS: MAGNESIUM OXIDE 400 mg/1 1
INACTIVE INGREDIENTS: COLLOIDAL SILICON DIOXIDE; CROSCARMELLOSE SODIUM; CELLULOSE, MICROCRYSTALLINE; STEARIC ACID

Magnesium Oxide Tablets

ACTIVE INGREDIENTS

Magnesium Oxide 400mg (241.3mg elemental magnesium)

Purposes

Antacid

USES

Relieves: (acid indigestion (upset stomach

WARNINGS

Do Not Use

Do not take more than 2 tablets in a 24 hour period or use the maximum dosage of this product for more than two weeks, except under the advice and supervision of a physician. May have a laxative effect.

Ask a Doctor if you have:

Kidney disease

Ask a Doctor/Pharmacist before use if you are:

Taking a prescription drug. Antacids may interact with certain prescription drugs.

Pregnancy or Breast Feeding

If pregnant or breast feeding, ask a health professional before use.

DIRECTIONS

Antacid Directions: (take 1 tablet twice a day or as directed by a physician

Magnesium Supplement Directions: (take 1 to 2 tablets daily or as directed by a physician

OTHER INFORMATION

(store at room temperature 59°-86° F (15°-30°C) (do not use if imprinted safety seal under cap is broken or missing (Magnesium content per tablet: 240 mg

INACTIVE INGREDIENTS

Colloidal silicon dioxide, croscarmellose sodium, microcrystalline cellulose, stearic acid

PACKAGE LABEL

Label Image for 400mg